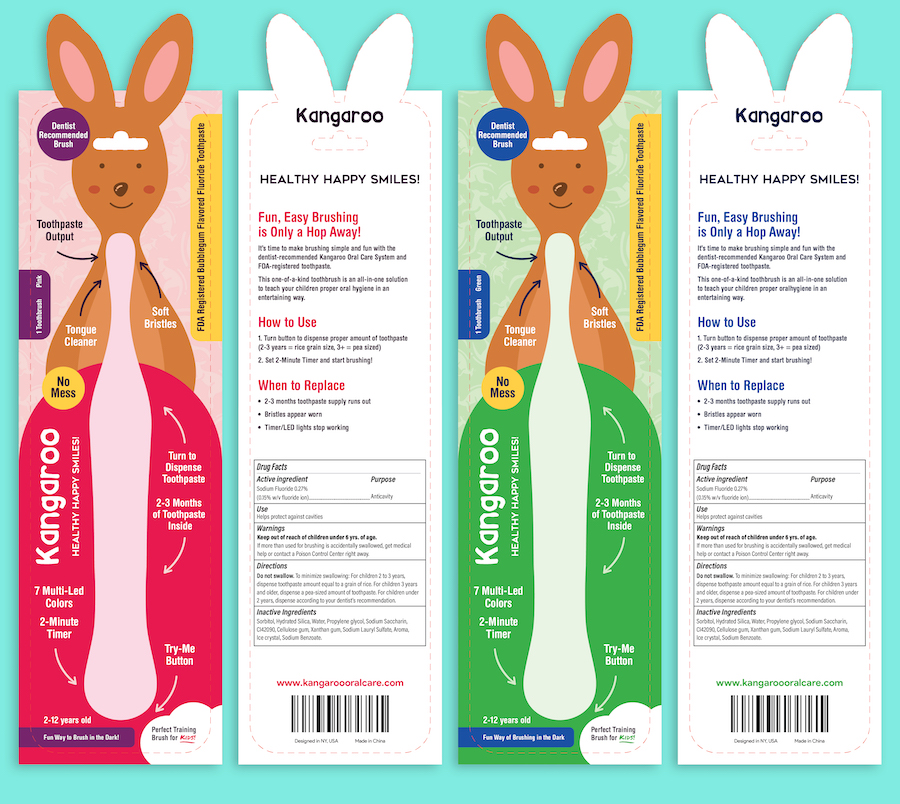 DRUG LABEL: KangarooOralCareToothpaste
NDC: 72840-1901 | Form: PASTE
Manufacturer: Kangaroo Oral Care, LLC
Category: otc | Type: HUMAN OTC DRUG LABEL
Date: 20190131

ACTIVE INGREDIENTS: SODIUM FLUORIDE 0.24 g/100 g
INACTIVE INGREDIENTS: XANTHAN GUM; SODIUM BENZOATE; SORBITOL, L-; WATER; SILICON DIOXIDE; PROPYLENE GLYCOL; DISODIUM CARBOXYMETHYLARSONATE; SODIUM LAURYL SULFATE; CARBOXYMETHYLCELLULOSE SODIUM, UNSPECIFIED FORM; SACCHARIN SODIUM

Kanagaroo Toothbrush Kit

Active Ingredient

sodium fluoride 0.24%（0.14% w/v fluoride ion）

Purpose

Anticavitytoothpaste

Use

helps aid in the prevention of dental cavities.

Warning

Keep out of reach of children under 6 years of age.
If more than used for brushing is accidently swallowed get medical help or contact a poison control center right away.

Directions

Adults and children 6 years of age and older:brush teeth thoroughly, after meals or at least twice a day or use as directed by a dentist.

do not swallow

to minimize swallowing use a pea-sized amount in children under 6

supervise children as necessary until capable of using without supervision

Keep out of reach of children under 6 years of age